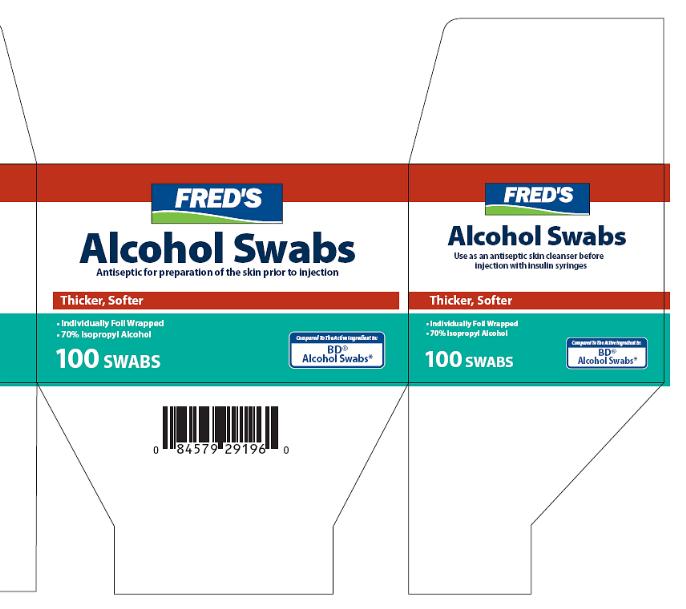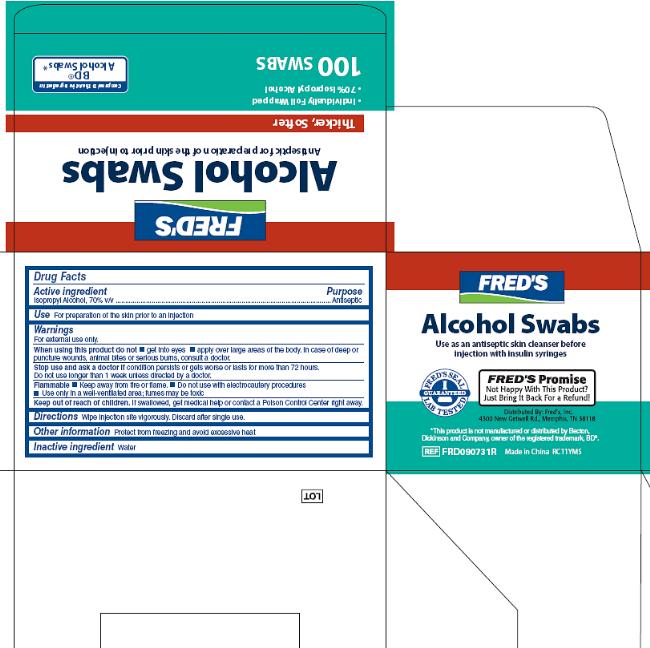 DRUG LABEL: Alcohol
NDC: 55315-809 | Form: SWAB
Manufacturer: Fred's Inc.
Category: otc | Type: HUMAN OTC DRUG LABEL
Date: 20121218

ACTIVE INGREDIENTS: ISOPROPYL ALCOHOL 70 mL/100 mL
INACTIVE INGREDIENTS: WATER

Drug Facts

Active ingredient

Isopropyl alcohol, 70% v/v

Purpose

Antiseptic

Uses

For preparation of the skin prior to injection

Warnings

For external use only.

When using this product

- Do not get into eyes
- apply over large areas of the body. In case of deep or puncture wounds, animal bites or serious burns, consult a doctor.

Stop use and ask a doctor if

- condition persists or gets worse or lasts for more than 72 hours
- do not use longer than 1 week unless directed by a doctor

Flammable

- Keep away from fire or flame
- Do not use with electrocautery procedures
- Use only in a well-ventilated area, fumes may be toxic

Keep out of reach of children.

If swallowed, get medical help or contact a Poison Control Center right away.

Directions

Wipe injection site vigorously. Discard after single use.

Other information

Protect from freezing and avoid excessive heat.

Inactive ingredients

Water

Package/Label Principal Display Panel

FRED'S

Alcohol Swabs

Antiseptic for preparation of the skin prior to injection

Thicker, Softer

- Individually Foil Wrapped
- 70% Isopropyl Alcohol

100 SWABS

Package/Label Back

Fred's Alcohol Swabs Box Top, Back, Side, Bottom